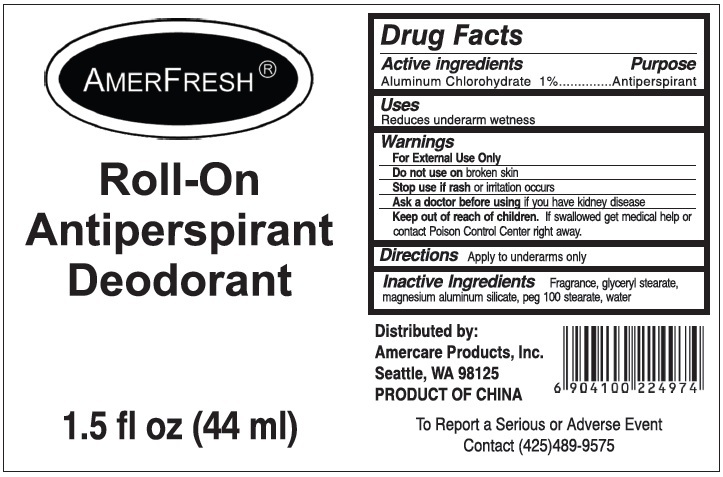 DRUG LABEL: AMERFRESH ROLL-ON ANTIPERSPIRANT DEODORANT
NDC: 51460-4974 | Form: LIQUID
Manufacturer: Amercare Products, Inc
Category: otc | Type: HUMAN OTC DRUG LABEL
Date: 20181218

ACTIVE INGREDIENTS: ALUMINUM CHLOROHYDRATE 10 mg/1 mL
INACTIVE INGREDIENTS: GLYCERYL STEARATE SE; MAGNESIUM ALUMINUM SILICATE; PEG-100 STEARATE; WATER

AMERFRESH ROLL-ON ANTIPERSPIRANT DEODORANT

DRUG FACTS

Active Ingredients Purpose

Aluminum Chlorohydrate 1% Antiperspirant

Purpose

Antiperspirant

Uses

Reduces underarm wetness

WARNINGS

For external use only

Do not use on broken skin

Stop use if rash or irritation occurs

Ask a doctor before using if you have kidney disease

Keep out of reach of children. If swallowed, get medical help or contact Poison Control Center right away.

DOSAGE AND ADMINISTRATION

DIRECTIONS: apply to underarms only.

INACTIVE INGREDIENTS:

Fragrance, Glyceryl stearate, magnesium aluminum silicate, peg100 stearate, water

Distributed by:

Amercare Products, Inc.

Seattle, WA 98125

PRODUCT OF CHINA

To report a serious or adverse event

Contact (425) 489-9575

PACKAGE LABEL

AMERFRESH

ROLL-ON ANTIPERSPIRANT DEODORANT

1.5 fl. oz (44ml)